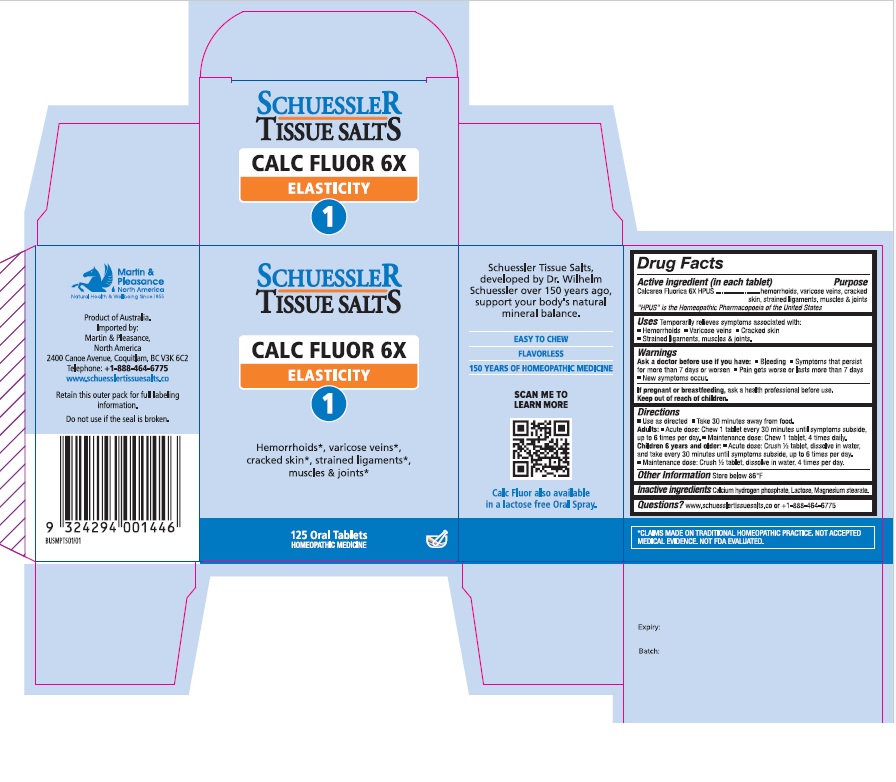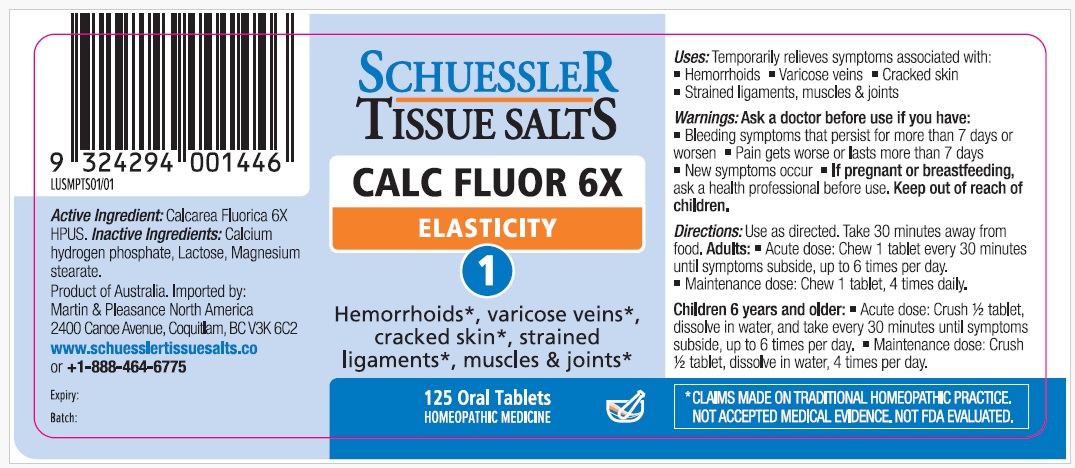 DRUG LABEL: Schuessler Tissue Salts Calc Fluor Elasticity 1
NDC: 84999-013 | Form: TABLET, CHEWABLE
Manufacturer: Martin & Pleasance Pty Ltd
Category: homeopathic | Type: HUMAN OTC DRUG LABEL
Date: 20250718

ACTIVE INGREDIENTS: CALCIUM FLUORIDE 6 [hp_X]/1 1
INACTIVE INGREDIENTS: LACTOSE MONOHYDRATE; MAGNESIUM STEARATE; ANHYDROUS DIBASIC CALCIUM PHOSPHATE

Active Ingredients Purpose

Calcarea fluorica 6X HPUS hemorrhoids, varicose veins, cracked skin, strained ligaments, muscles & joints

" HPUS" is the Homeopathic Pharmacopoeia of the United States

Uses

Temporarily relieves symptoms associated with

- Hemorrhoids
- Varicose veins
- Cracked skin
- Strained ligaments, muscles and joints

Warnings

Ask a doctor before use if you have:

- Bleeding
- Symptoms lhat persist for more than 7 days or worsen
- Pain gets worse or lasts more than 7 days
- New symptoms occur.

If pregnant or breastfeeding, ask a health professional before use. Keep out of reach of children.

Directions

- Use as directed
- Take 30 minutes away from food

Adults: Acute dose: Chew 1 tablet every 30 minutes until symptoms subside up to 6 times per day.

Maintenance dose: Chew 1 tablet, 4 times daily.

Children 6 years and older: Acute dose: Crush 1/2 tablet, dissolve in water, and take every 30 minutes until symptoms subside, up to six times per day.

Maintenance dose :Crush 1/2 tablet, dissolve in water, 4 times per day.

Other Information

Store below 86°F

Inactive Ingredients

Calcium hydrogen phosphate, Lactose, Magnesium stearate

Questions?www.schuesslertissuesalts.co or + 1-888-464-6775